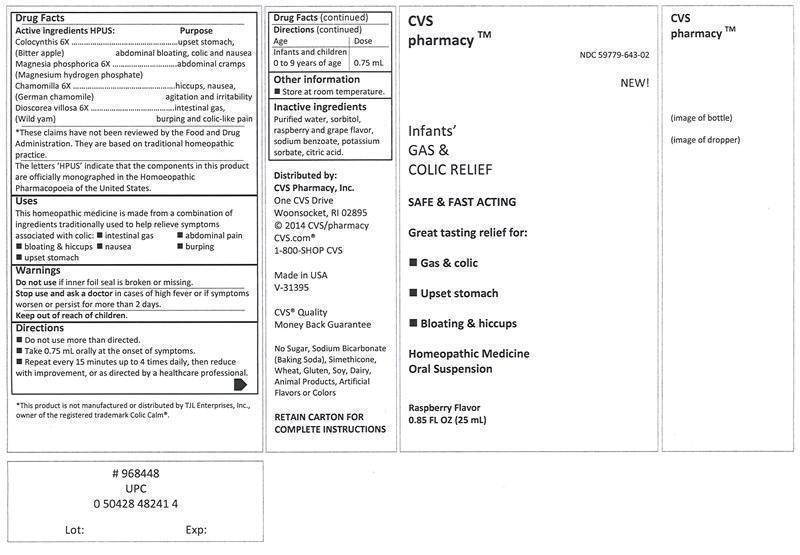 DRUG LABEL: INFANTS GAS AND COLIC RELIEF
NDC: 63388-643 | Form: LIQUID
Manufacturer: Laboratoire Atlas Inc
Category: homeopathic | Type: HUMAN OTC DRUG LABEL
Date: 20251008

ACTIVE INGREDIENTS: CITRULLUS COLOCYNTHIS FRUIT PULP 6 [hp_X]/25 mL; MAGNESIUM PHOSPHATE, DIBASIC 6 [hp_X]/25 mL; CHAMOMILE 6 [hp_X]/25 mL; DIOSCOREA VILLOSA ROOT 6 [hp_X]/25 mL
INACTIVE INGREDIENTS: WATER; SORBITOL; SODIUM BENZOATE; POTASSIUM SORBATE; CITRIC ACID MONOHYDRATE

Drug Facts

Active ingredients HPUS*

Colocynthis (Bitter apple) 6X

Magnesia phosphorica (Magnesium hydrogen phosphate) 6X

Chamomilla (German chamomile) 6X

Dioscorea villosa (Wild yam) 6X

*The letters "HPUS" indicate that the components in this product are officially monographed in the Homoeopathic Pharmacopoeia of the United States.

Purpose

Colocynthis (Bitter apple) 6X.......................................................................upset stomach, abdominal bloating, colic and nausea

Magnesia phosphorica (Magnesium hydrogen phosphate) 6X...........................abdominal cramps

Chamomilla (German chamomile) 6X............................................................hiccups, nausea, agitation and irritability

Dioscorea villosa (Wild yam) 6X...................................................................intestinal gas, burping and colic-like pain

Uses

This homeopathic medicine is made from a combination of ingredients traditionnally used to help relieve symptoms associated with colic:

• intestinal gas

• abdominal pain

• bloating & hiccups

• nausea

• burping

• upset stomach

*These claims have not been reviewed by the Food and Drug Administration. They are based on traditional homeopathic practice.

Warnings

Do not use if inner foil seal is broken or missing.

Stop use and ask a doctor in cases of high fever or if symptoms worsen or persist for more than 2 days.

Keep out of reach of children.

Directions

• Do not use more than directed.

• Take 0.75 mL orally at the onset of symptoms.

• Repeat every 15 minutes up to 4 times daily, then reduce with improvement or as directed by a healthcare professional.

Age Dose

Infants and children 0 to 9 years of age 0.75 mL

Other information

Store at room temperature.

Inactive ingredients

Purified water, sorbitol, raspberry and grape flavor, sodium benzoate, potassium sorbate, citric acid.